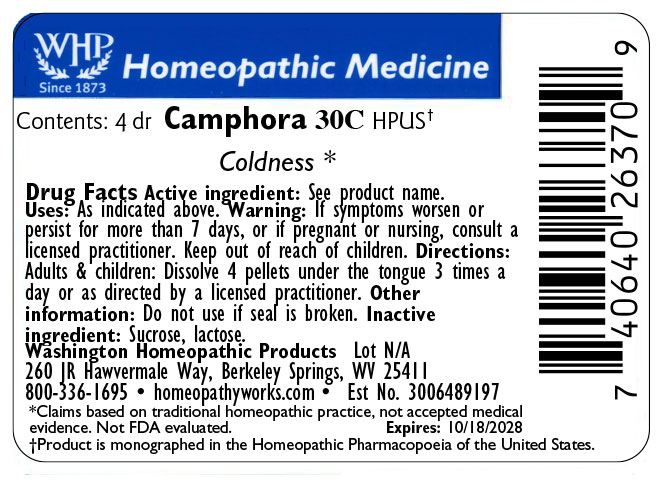 DRUG LABEL: Camphora
NDC: 71919-811 | Form: PELLET
Manufacturer: Washington Homeopathic Products
Category: homeopathic | Type: HUMAN OTC DRUG LABEL
Date: 20250128

ACTIVE INGREDIENTS: CAMPHOR (NATURAL) 30 [hp_C]/1 1
INACTIVE INGREDIENTS: LACTOSE; SUCROSE

Camphora

ACTIVE INGREDIENT

CAMPHORA

USES

Indicated for coldness

KEEP OUT OF REACH OF CHILDREN

As with all medicines, keep out of reach of children.

INDICATIONS

CAMPHORA Coldness

STOP USE AND ASK DOCTOR

If symptoms worsen or persist for more than 7 days, or if pregnant or nursing, consult a licensed practitioner.

DIRECTIONS

Directions: Adults & children: Dissolve 4 pellets under the tongue 3 times a day or as directed by a licensed practitioner. Other information: Do not use if seal is broken.

INACTIVE INGREDIENTS

SUCROSE/LACTOSE

PACKAGE LABEL

The OTC potency range of CAMPHORA is 30c - 200c.

Availability is subject to change.

All WHP single remedies are made to order; thus the labels are printed on the same label stock as the orders are filled.